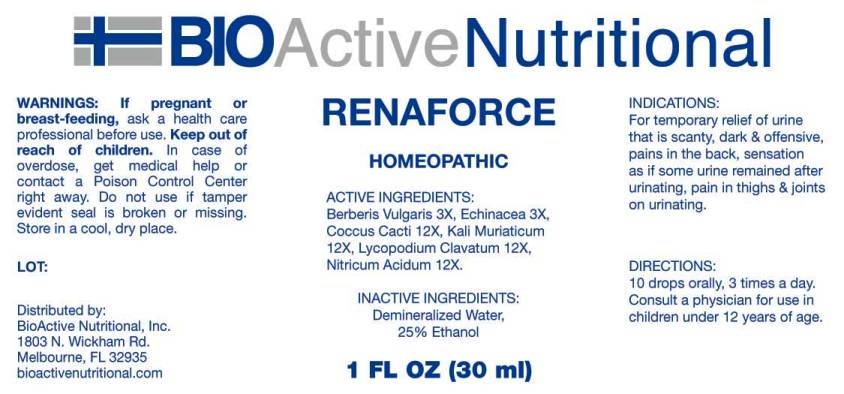 DRUG LABEL: RENAFORCE
NDC: 43857-0340 | Form: LIQUID
Manufacturer: BioActive Nutritional, Inc.
Category: homeopathic | Type: HUMAN OTC DRUG LABEL
Date: 20161206

ACTIVE INGREDIENTS: BERBERIS VULGARIS ROOT BARK 3 [hp_X]/1 mL; ECHINACEA ANGUSTIFOLIA 3 [hp_X]/1 mL; PROTORTONIA CACTI 12 [hp_X]/1 mL; POTASSIUM CHLORIDE 12 [hp_X]/1 mL; LYCOPODIUM CLAVATUM SPORE 12 [hp_X]/1 mL; NITRIC ACID 12 [hp_X]/1 mL
INACTIVE INGREDIENTS: WATER; ALCOHOL

Drug Facts:

ACTIVE INGREDIENTS:

Berberis Vulgaris 3X, Echinacea (Angustifolia) 3X, Coccus Cacti 12X, Kali Muriaticum 12X, Lycopodium Clavatum 12X, Nitricum Acidum 12X.

INDICATIONS:

For temporary relief of urine that is scanty, dark & offensive, pains in the back, sensation as if some urine remained after urinating, pain in thighs & joints on urinating.

WARNINGS:

If pregnant or breast-feeding, ask a health care professional before use

Keep out of reach of children. In case of overdose, get medical attention or contact a Poison Control Center right away.

Do not use if tamper evident seal is broken or missing. Store in a cool, dry place.

Keep out of reach of children. In case of overdose, get medical attention or contact a Poison Control Center right away.

DIRECTIONS:

10 drops orally, 3 times a day. Consult a physician for use in children under 12 years of age.

INDICATIONS:

For temporary relief of urine that is scanty, dark & offensive, pains in the back, sensation as if some urine remained after urinating, pain in thighs & joints on urinating.

INACTIVE INGREDIENTS:

Demineralized Water, 25% Ethanol

QUESTIONS:

Distributed by:
BioActive Nutritional, Inc.
1803 N. Wickham Rd.
Melbourne, FL 32935
bioactivenutritional.com

PACKAGE LABEL DISPLAY:

BIOActive Nutritional

RENAFORCE

HOMEOPATHIC

1 FL OZ (30 ml)